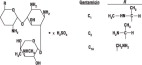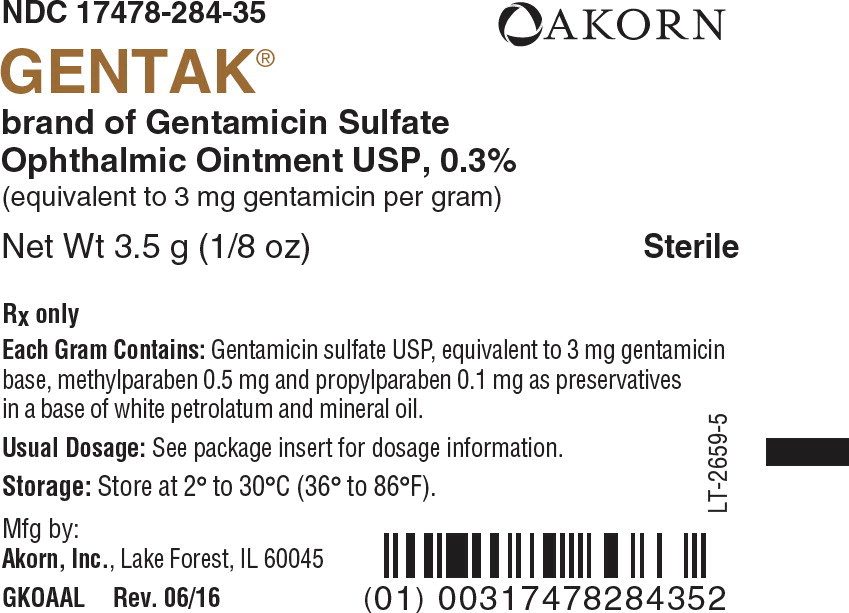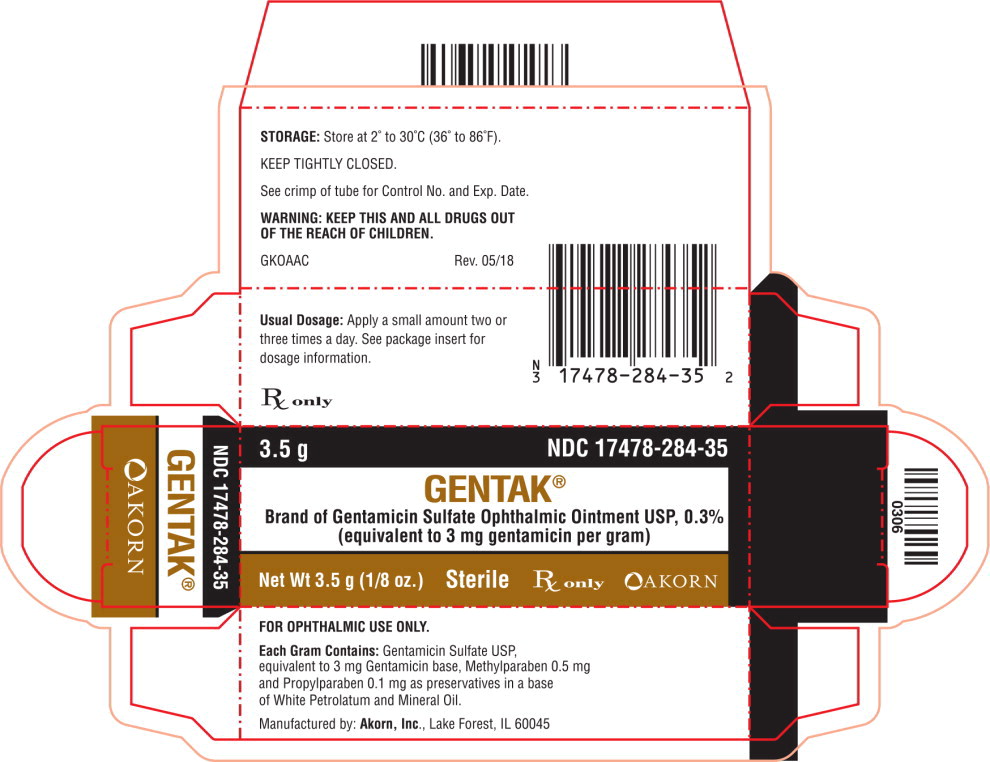 DRUG LABEL: Gentak
NDC: 67296-0114 | Form: OINTMENT
Manufacturer: Redpharm Drug
Category: prescription | Type: HUMAN PRESCRIPTION DRUG LABEL
Date: 20240612

ACTIVE INGREDIENTS: GENTAMICIN SULFATE 3 mg/1 g
INACTIVE INGREDIENTS: METHYLPARABEN 0.5 mg/1 g; PROPYLPARABEN 0.1 mg/1 g; PETROLATUM; MINERAL OIL

GENTAK®
Gentamicin Sulfate
Ophthalmic Ointment USP,0.3%

Sterile

Rx only

DESCRIPTION

GENTAK®Gentamicin sulfate is a water soluble antibiotic of the aminoglycoside group.

Gentamicin sulfate ophthalmic ointment is a sterile ointment for ophthalmic use. Each gram contains gentamicin sulfate equivalent to 3 mg gentamicin in a base of white petrolatum and mineral oil, with methylparaben and propylparaben as preservatives.

Gentamicin is obtained from cultures of Micromonospora purpurea.It is a mixture of the sulfate salts of gentamicin C1C2, and C1A. All three components appear to have similar antimicrobial activities. Gentamicin sulfate occurs as a white to buff powder and is soluble in water and insoluble in alcohol. The structural formula is as follows:

CLINICAL PHARMACOLOGY

MICROBIOLOGY

Microbiology:Gentamicin sulfate is active in vitroagainst many strains of the following microorganisms:

- Staphylococcus aureus, Staphylococcus epidermidis, Streptococcus pyogenes, Streptococcus pneumoniae, Enterobacter aerogenes, Escherichia coli, Haemophilus influenzae, Klebsiella pneumoniae, Neisseria gonorrhoeae, Pseudomonas aeruginosa, and Serratia marcescens.

INDICATIONS AND USAGE

Gentamicin sulfate ophthalmic ointment is indicated in the topical treatment of ocular bacterial infections including conjunctivitis, keratitis, keratoconjunctivitis, corneal ulcers, blepharitis, blepharonconjunctivitis: acute meibomianitis, and dacryocystitis, caused by susceptible strains of the following microorganisms:

- Staphylococcus aureus, Staphylococcus epidermidis, Streptococcus pyogenes, Streptococcus pneumoniae, Enterobacter aerogenes, Escherichia coli, Haemophilus influenzae, Klebsiella pneumoniae, Neisseria gonorrhoeae, Pseudomonas aeruginosa, and Serratia marcescens.

CONTRAINDICATIONS

Gentamicin sulfate ophthalmic ointment is con-traindicated in patients with known hypersensitivity to any of the components.

WARNINGS

NOT FOR INJECTION INTO THE EYE.

Gentamicin sulfate ophthalmic ointment is not for injection. It should never be injected subconjunctivally, nor should it be directly introduced into the anterior chamber of the eye.

PRECAUTIONS

GENERAL PRECAUTIONS

General:Prolonged use of topical antibiotics may give rise to overgrowth of nonsusceptible organisms including fungi. Bacterial resistance to gentamicin may also develop. If purulent discharge, inflammation or pain becomes aggravated, the patient should discontinue use of the medication and consult a physician.

If irritation or hypersensitivity to any component of the drug develops, the patient should discontinue use of this preparation and appropriate therapy should be instituted.

Ophthalmic ointments may retard corneal healing.

PATIENT COUNSELING INFORMATION

Information for patients:To avoid contamination, do not touch tip of container to the eye, eyelid or any surface.

CARCINOGENESIS AND MUTAGENESIS AND IMPAIRMENT OF FERTILITY

Carcinogenesis, Mutagenesis, Impairment of Fertility:There are no published carcinogenicity or impairment of fertility studies on gentamicin. Aminoglycoside antibiotics have been found to be non-mutagenic.

PREGNANCY

Pregnancy:Pregnancy Category C. Gentamicin has been shown to depress body weights, kidney weights and median glomerular counts in newborn rats when administered systemically to pregnant rats in daily doses approximately 500 times the maximum recommended ophthalmic human dose. There are no adequate and well-controlled studies in pregnant women. Gentamicin should be used during pregnancy only if the potential benefit justifies the potential risk to the fetus.

PEDIATRIC USE

Pediatric Use:Safety and effectiveness in neonates have not been established.

ADVERSE REACTIONS

Bacterial and fungal corneal ulcers have developed during treatment with gentamicin ophthalmic preparations.

The most frequently reported adverse reactions are ocular burning and irritation upon drug instillation, non-specific conjunctivitis, conjunctival epithelial defects and conjunctival hyperemia.

Other adverse reactions which have occurred rarely are allergic reactions, thrombocytopenic purpura and hallucinations.

DOSAGE AND ADMINISTRATION

Apply a small amount (approximately 1/2 inch ribbon) of ointment to the affected eye(s) two or three times a day.

HOW SUPPLIED

GENTAK®Gentamicin sulfate ophthalmic ointment USP, 0.3% is supplied in 3.5 g tube, box of one.

(NDC 17478-284-35)

STORAGE AND HANDLING

STORAGE:Store at 2° to 30°C (36° to 86°F).

Akorn
Manufactured by: Akorn, Inc.
Lake Forest, IL 60045
GKO00N Rev. 06/16

Principal Display Panel Text for Container Label:

NDC 17478-284-35 Akorn Logo

Gentak®

brand of Gentamicin Sulfate

Ophthalmic Ointment USP, 0.3%

(equivalent to 3 mg gentamicin per gram)

Net Wt 3.5 g (1/8 oz) Sterile

Rx only

Principal Display Panel Text for Carton Label:

3.5 g NDC 17478-284-35

Gentak®

Brand of Gentamicin Sulfate Ophthalmic Ointment USP, 0.3%

(equivalent to 3 mg gentamicin per gram)

Net Wt 3.5 g (1/8 oz.) Sterile Rx only Akorn Logo